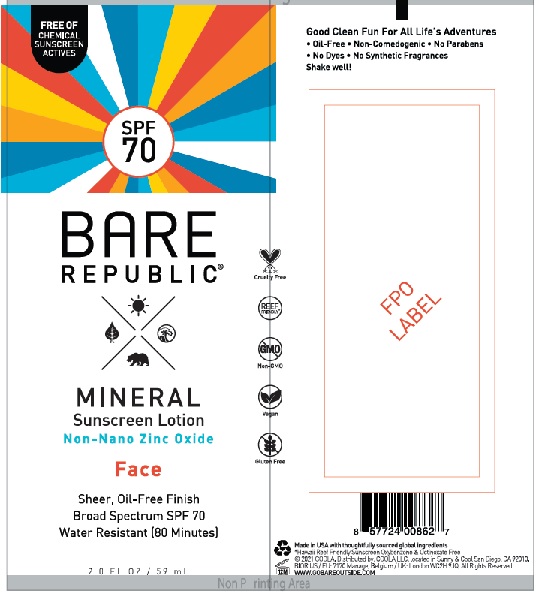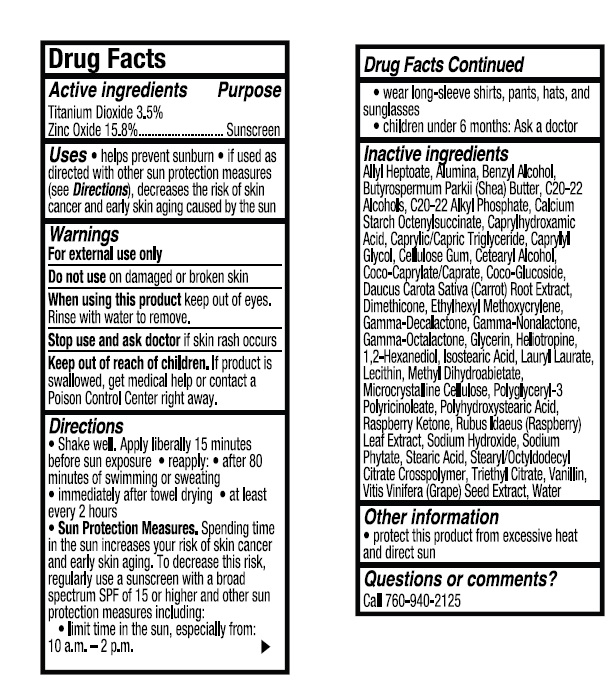 DRUG LABEL: Coola Bare Republic Mineral Face-Lotion
NDC: 79753-041 | Form: LOTION
Manufacturer: COOLA LLC
Category: otc | Type: HUMAN OTC DRUG LABEL
Date: 20231220

ACTIVE INGREDIENTS: ZINC OXIDE 15.8 g/100 mL; TITANIUM DIOXIDE 3.5 g/100 mL
INACTIVE INGREDIENTS: ALLYL HEPTANOATE; BENZYL ALCOHOL; BUTYROSPERMUM PARKII (SHEA) BUTTER UNSAPONIFIABLES; C20-22 ALCOHOLS; C20-22 ALKYL PHOSPHATE; CAPRYLHYDROXAMIC ACID; MEDIUM-CHAIN TRIGLYCERIDES; CAPRYLYL GLYCOL; CARBOXYMETHYLCELLULOSE SODIUM, UNSPECIFIED; CETOSTEARYL ALCOHOL; COCO-CAPRYLATE/CAPRATE; COCO GLUCOSIDE; CARROT; DIMETHICONE; ETHYLHEXYL METHOXYCRYLENE; .GAMMA.-DECALACTONE; .GAMMA.-NONALACTONE; .GAMMA.-OCTALACTONE; GLYCERIN; PIPERONAL; 1,2-HEXANEDIOL; ISOSTEARIC ACID; LAURYL LAURATE; LECITHIN, SUNFLOWER; METHYL DIHYDROABIETATE; MICROCRYSTALLINE CELLULOSE; POLYGLYCERYL-3 PENTARICINOLEATE; POLYHYDROXYSTEARIC ACID (2300 MW); 4-(P-HYDROXYPHENYL)-2-BUTANONE; RUBUS IDAEUS LEAF; SODIUM HYDROXIDE; DISODIUM PHTHALATE; STEARIC ACID; STEARYL/OCTYLDODECYL CITRATE CROSSPOLYMER; TRIETHYL CITRATE; VANILLIN; VITIS VINIFERA SEED; WATER

Coola Bare Republic Mineral Face Lotion SPF 70

Drug Facts

Active Ingredients

Titanium Dioxide 3.5%

Zinc Oxide 15.8%

Purpose

Suncreen

INDICATIONS AND USAGE

Uses • helps prevent sunburn • if used as

directed with other sun protection measures

(see Directions), decreases the risk of skin

cancer and early skin aging caused by the sun

Warnings

For external use only

Do not use on damaged or broken skin

When using this product keep out of eyes. Rinse with water to remove.

Stop use and ask doctor if skin rash occurs

Keep out of reach of children. If product is

swallowed, get medical help or contact a

Poison Control Center right away.

Directions
● Shake well. Apply liberally 15 minutes
before sun exposure ● reapply: ● after 80
minutes of swimming or sweating
● immediately after towel drying ● at least
every 2 hours
● Sun Protection Measures. Spending time
in the sun increases your risk of skin cancer
and early skin aging. To decrease this risk,
regularly use a sunscreen with a broad
spectrum SPF of 15 or higher and other sun
protection measures including:
● limit time in the sun, especially from:
10 a.m. - 2 p.m.
● wear long-sleeve shirts, pants, hats, and
sunglasses
●Children under 6 months: Ask a doctor

Inactive Ingredients
Allyl Heptoate, Alumina, Benzyl Alcohol,
Butyrospermum Parkii (Shea) Butter, C20-22
Alcohols, C20-22 Alkyl Phosphate, Calcium
Starch Octenylsuccinate, Caprylhydroxamic
Acid, Caprylic/Capric Triglyceride, Caprylyl
Glycol, Cellulose Gum, Cetearyl Alcohol,
Coco-Caprylate/Caprate, Coco-Glucoside,
Daucus Carota Sativa (Carrot) Root Extract,
Dimethicone, Ethylhexyl Methoxycrylene,
Gamma-Decalactone, Gamma-Nonalactone,
Gamma-Octalactone, Glycerin, Heliotropine,
1,2-Hexanediol, Isostearic Acid, Lauryl Laurate,
Lecithin, Methyl Dihydroabietate,
Microcrystalline Cellulose, Polyglyceryl-3
Polyricinoleate, Polyhydroxystearic Acid,
Raspberry Ketone, Rubus Idaeus (Raspberry)
Leaf Extract, Sodium Hydroxide, Sodium
Phytate, Stearic Acid, Stearyl/Octyldodecyl
Citrate Crosspolymer, Triethyl Citrate, Vanillin,
Vitis Vinifera (Grape) Seed Extract, Water

Other information

- protect this product from excessive heat and direct sun

Questions or comments?
Call 760-940-2125

COOLA Label

SPF

70

BARE

REPUBLIC

MINERAL

Sunscreen Lotion

Non-Nano Zinc Oxide

Face

Sheer, Oil-Free Finish

Broad Spectrum SPF 70

Water Resistant (80 Minutes)

2.0 FL OZ / 59 mL

*Hawaii Reef Friendly Sunscreen Oxybenzone & Octinoxate Free
©2021 COOLA. Distributed by: COOLA LLC, located in Sunny & Cool

San Diego, CA 92010.

res